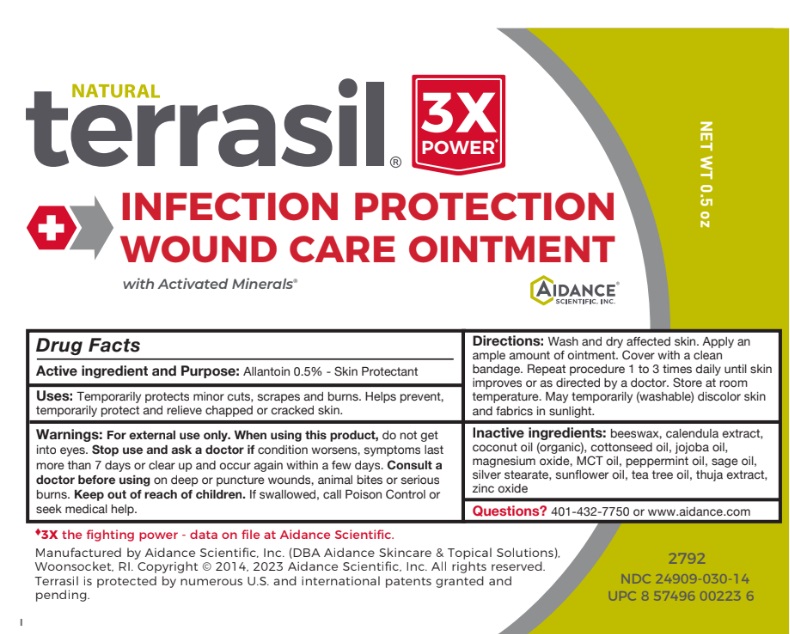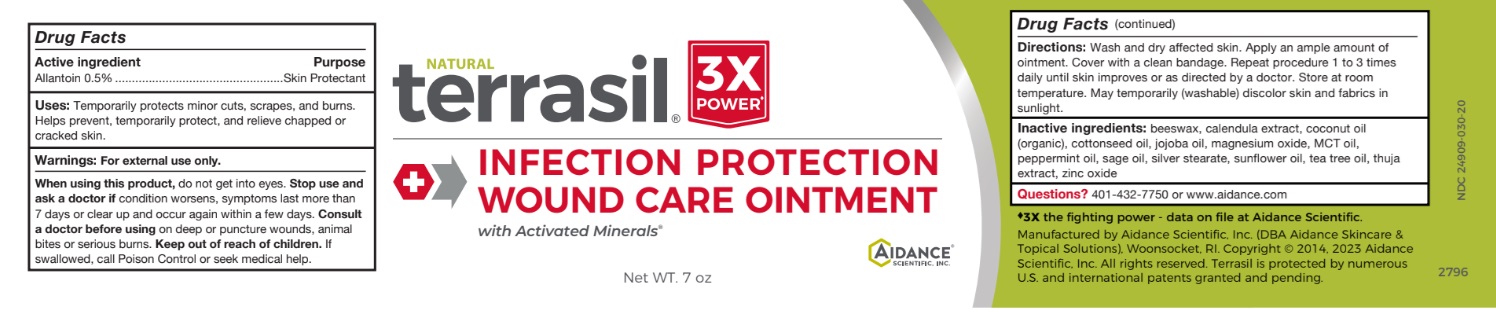 DRUG LABEL: terrasil Infection Protection Wound Care
NDC: 24909-030 | Form: OINTMENT
Manufacturer: Aidance Scientific, Inc, DBA Aidance Skincare & Topical Solutions
Category: otc | Type: HUMAN OTC DRUG LABEL
Date: 20250711

ACTIVE INGREDIENTS: ALLANTOIN 0.5 g/100 g
INACTIVE INGREDIENTS: YELLOW WAX; CALENDULA OFFICINALIS FLOWER; COCONUT OIL; COTTONSEED OIL; JOJOBA OIL; MAGNESIUM OXIDE; PALM OIL; PEPPERMINT OIL; SAGE OIL; SILVER STEARATE; SUNFLOWER OIL; TEA TREE OIL; THUJA OCCIDENTALIS LEAF; ZINC OXIDE

24909-030 terrasil Infection Protection Wound Care

Active Ingredient

Allantoin 0.5%

Purpose

Skin Protectant

Uses

Temporarily protects minor cuts, scrapes, and burns. Helps prevent, temporarily protect, and relieve chapped or cracked skin.

Warnings

For external use only. When using this product, do not get into eyes. Stop use and ask a doctor ifcondition worsens, symptoms last more than 7 days or clear up and occur again within a few days. Consult a doctor before usingon deep or puncture wounds, animal bites or serious burns. K eep out of reach of children.If swallowed, call Poison Control or seek medical help.

Directions

Wash and dry affected skin. Apply an ample amount of ointment. Cover with a clean bandage. Repeat procedure 1 to 3 times daily until skin improves or as directed by a doctor.

Inactive Ingredients

beeswax, calendula extract, coconut oil (organic), cottonseed oil, jojoba oil, magnesium oxide, MCT oil, peppermint oil, sage oil, silver stearate, sunflower oil, tea tree oil, thuja extract, zinc oxide

Other information

Store at room temperature. May temporarily (washable) discolor skin and fabrics in sunlight.